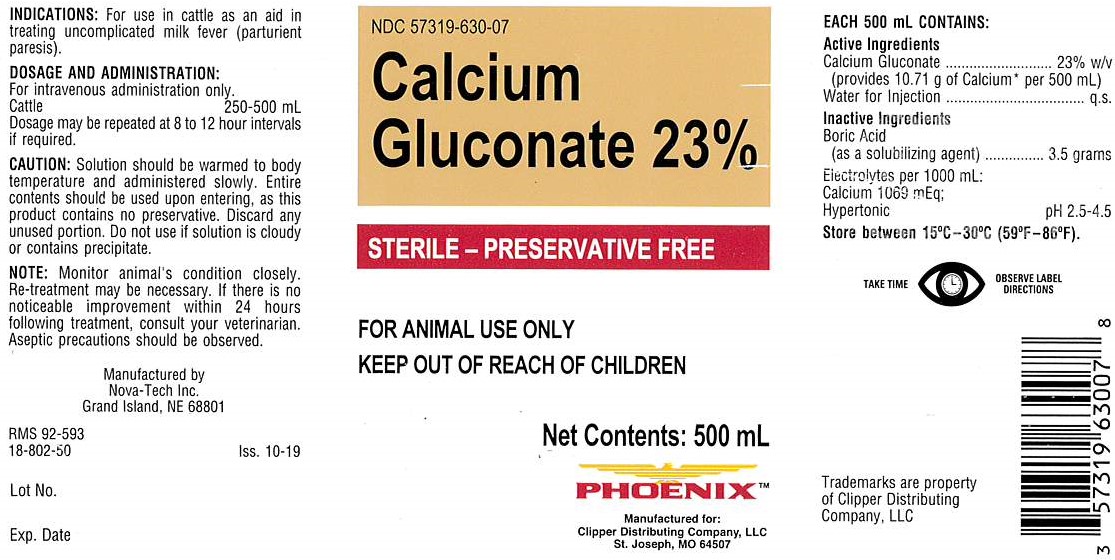 DRUG LABEL: Calcium Gluconate
NDC: 57319-630 | Form: INJECTION, SOLUTION
Manufacturer: Phoenix
Category: animal | Type: OTC ANIMAL DRUG LABEL
Date: 20191126

ACTIVE INGREDIENTS: CALCIUM GLUCONATE 23 g/100 mL

CALCIUM GLUCONATE 23%

INDICATIONS:

For use in cattle as an aid in treating uncomplicated milk fever (parturient paresis).

DOSAGE AND ADMINISTRATION:

For intravenous administrion only.

Cattle: 250 to 500 mL

Doasage may be repeated at 8 to 12 hour intervals if required.

PRECAUTIONS

TAKE TIME OBSERVE LABEL DIRECTIONS

INFORMATION FOR OWNERS/CAREGIVERS

Manufactured by

Nova-Tech Inc.

Grand Island, NE 68801

RMS 92-593

18-802-50

Iss. 10-19

Lot No.

Exp. Date

NDC 57319-630-07

Calcium Gluconate 23%

Sterile - Preservative Free

Next Contents: 500 mL

PhoenixTM

Manufactured for:

Clipper Distributing Company, LLC

St. Joseph, MO 64507

Trademarks are property

of Clipper Distributing

Company, LLC

ACTIVE INGREDIENT

Each 500 mL CONTAINS:

Active Ingredients

Calcium Gluconate...................23% w/v

(provides 10.71 g of Calcium * per 500 mL)

Water for Injection ......................... q.s.

Inactive Ingredients

Boric Acid
(as a solubilizing agent)...........3.5 grams
Electrolytes per 1000 mL:

Calcium 1069 mEq;
Hypertonic pH 2.5-4.5

STORAGE AND HANDLING

Store between 15°C-30°C (59°F-86°F).

GENERAL PRECAUTIONS

FOR ANIMAL USE ONLY

KEEP OUT OF REACH OF CHILDREN

Caution:

Solution should be warmed to body temperature and admisinstered slowly. Entire contents should be used upon entering, as this product contains no preservative. Discard any unused portion. Do no use if solution is cloudy or contains precipitate.

Note:

Monitor animal's condition closely. Re-treatment may be necessary. If there is no noticeable improvement within 24 hours following treatment, consult your veterinarian. Aseptic precautions should be observed.